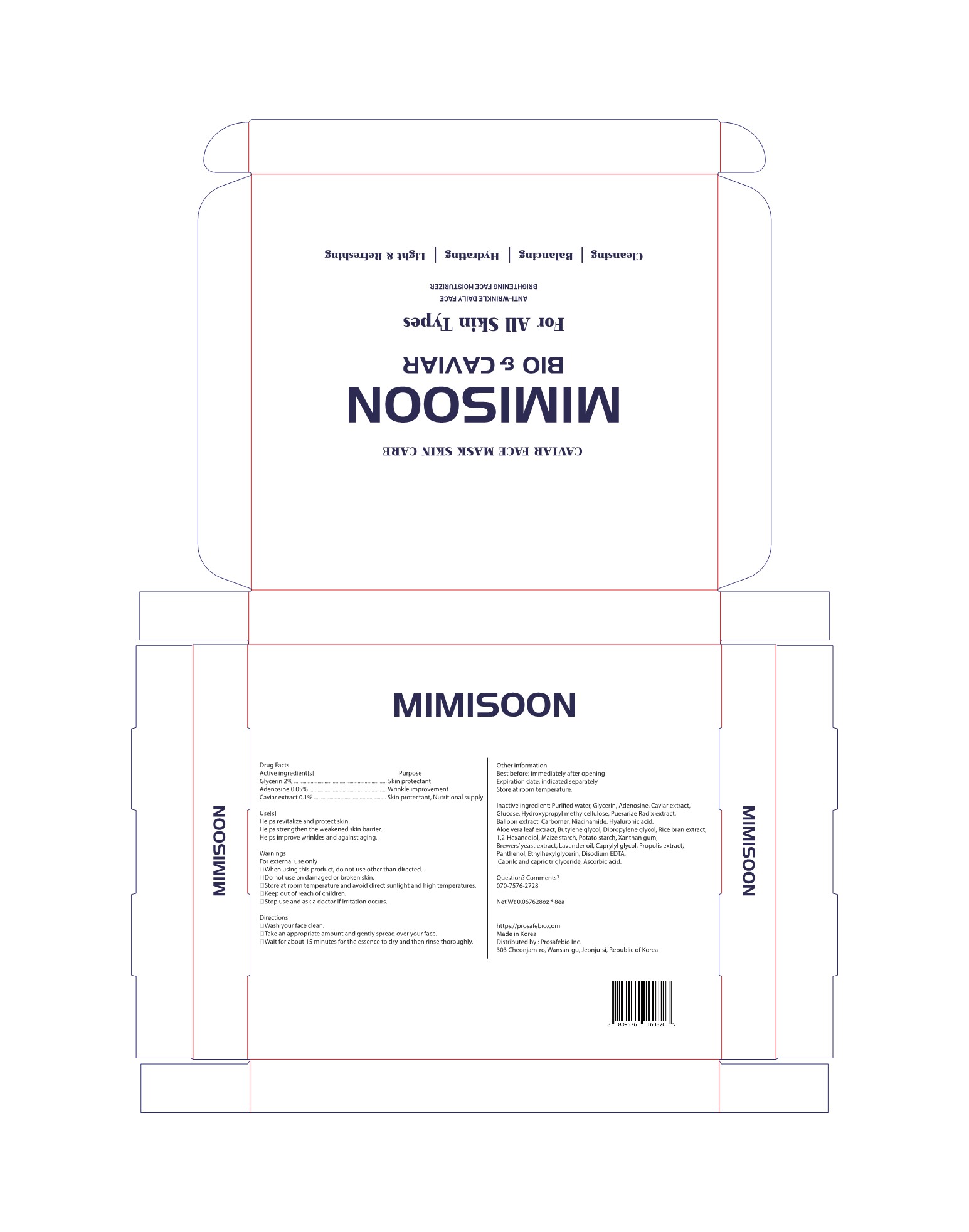 DRUG LABEL: MIMISOON
NDC: 81745-601 | Form: INJECTION, EMULSION
Manufacturer: PROSAFEBIO
Category: otc | Type: HUMAN OTC DRUG LABEL
Date: 20221018

ACTIVE INGREDIENTS: GLYCERIN 2 g/100 mL; ADENOSINE 0.05 g/100 mL; CAVIAR, UNSPECIFIED 0.1 g/100 mL
INACTIVE INGREDIENTS: PANTHENOL; EDETATE DISODIUM ANHYDROUS; PUERARIA MONTANA VAR. LOBATA ROOT; CARBOMER HOMOPOLYMER, UNSPECIFIED TYPE; ALOE VERA LEAF; RICE BRAN; HYPROMELLOSES; WATER; ANHYDROUS DEXTROSE; NIACINAMIDE; HYALURONIC ACID; BUTYLENE GLYCOL; DIPROPYLENE GLYCOL; 1,2-HEXANEDIOL; XANTHAN GUM; LAVENDER OIL; MEDIUM-CHAIN TRIGLYCERIDES; ASCORBIC ACID; STARCH, CORN; STARCH, POTATO; CAPRYLYL GLYCOL; SACCHAROMYCES CEREVISIAE; PROPOLIS WAX; ETHYLHEXYLGLYCERIN

81745-601 MIMISOON

Active ingredients

Glycerin 2%

Adenosine 0.05%

Caviar extract 0.1%

Purpose

Glycerin 2% ......................................................................................................... Skin protectant

Adenosine 0.05% ......................................................................................... Wrinkle improvement

Caviar extract 0.1% .................................................................... Skin protectant, Nutritional supply

Uses

Helps revitalize and protect skin.

Helps strengthen the weakened skin barrier.

Helps improve wrinkles and against aging.

Warnings

For external use only

◾Store at room temperature and avoid direct sunlight and high temperatures.

Warnings

When using this product, do not use other than directed.

Warnings

Stop use and ask a doctor if irritation occurs.

Warnings

Keep out of reach of children.

Warnings

Do not use on damaged or broken skin.

Directions

◾Wash your face clean.

◾Take an appropriate amount and gently spread over your face.

◾Wait for about 15 minutes for the essence to dry and then rinse thoroughly.

Inactive ingredients

Purified water, Glycerin, Adenosine, Caviar extract, Glucose, Hydroxypropyl methylcellulose, Puerariae Radix extract, Balloon extract, Carbomer, Niacinamide, Hyaluronic acid, Aloe vera leaf extract, Butylene glycol, Dipropylene glycol, Rice bran extract, 1,2-Hexanediol, Maize starch, Potato starch, Xanthan gum, Brewers’ yeast extract, Lavender oil, Caprylyl glycol, Propolis extract, Panthenol, Ethylhexylglycerin, Disodium EDTA, Caprilc and capric triglyceride, Ascorbic acid.

Display panel

81745-601